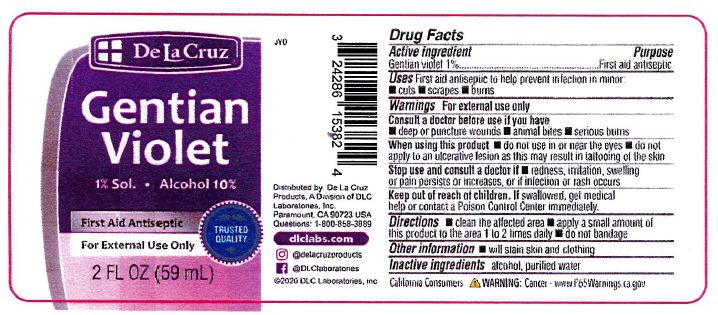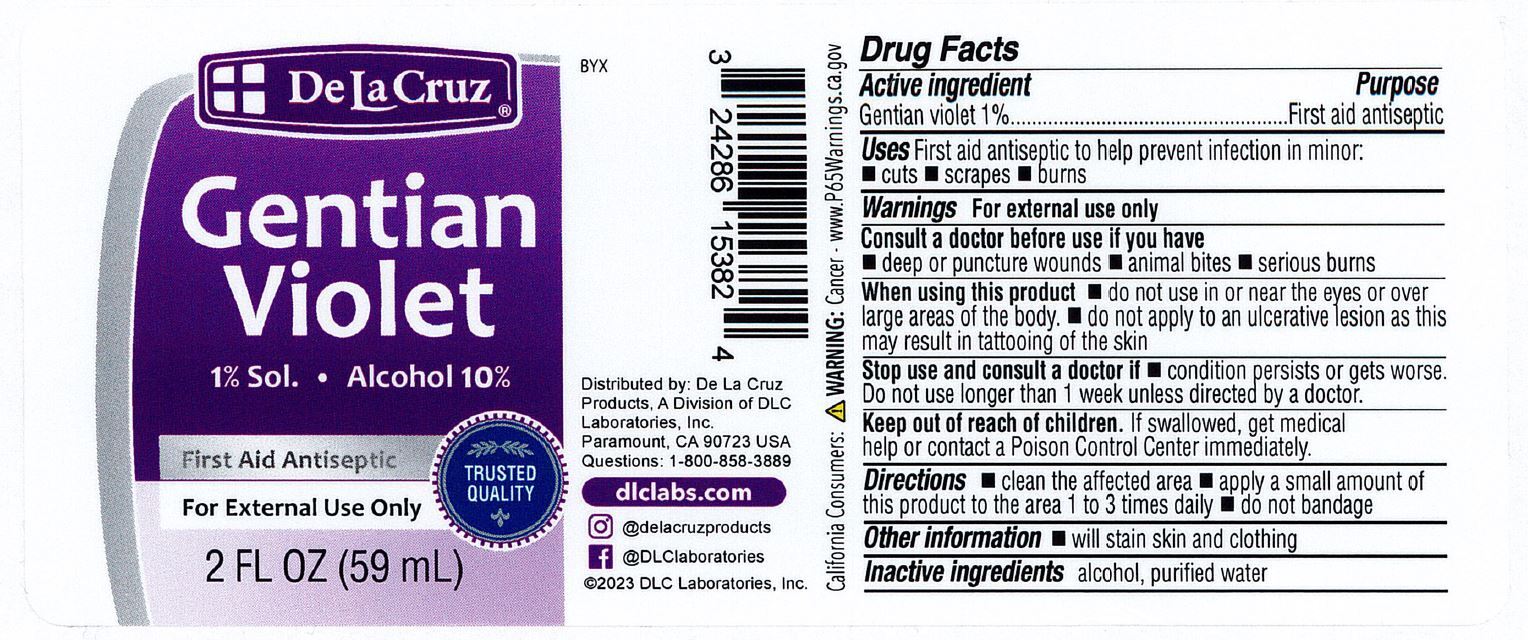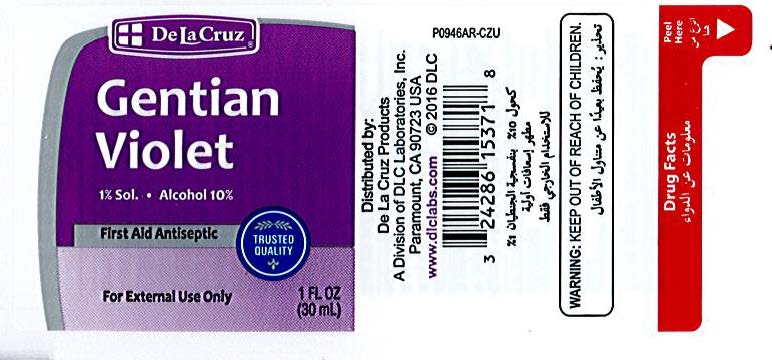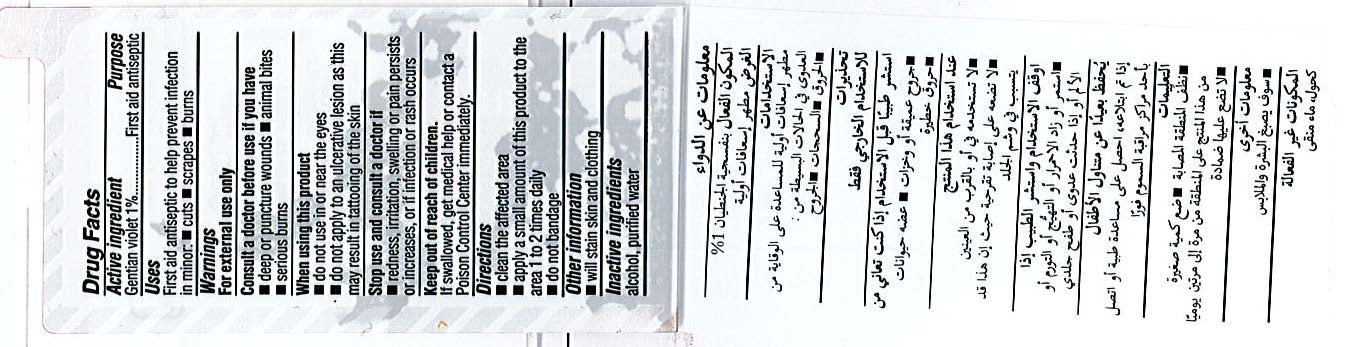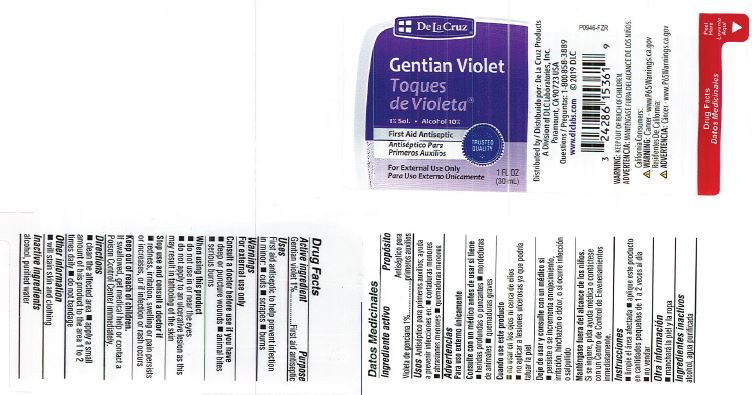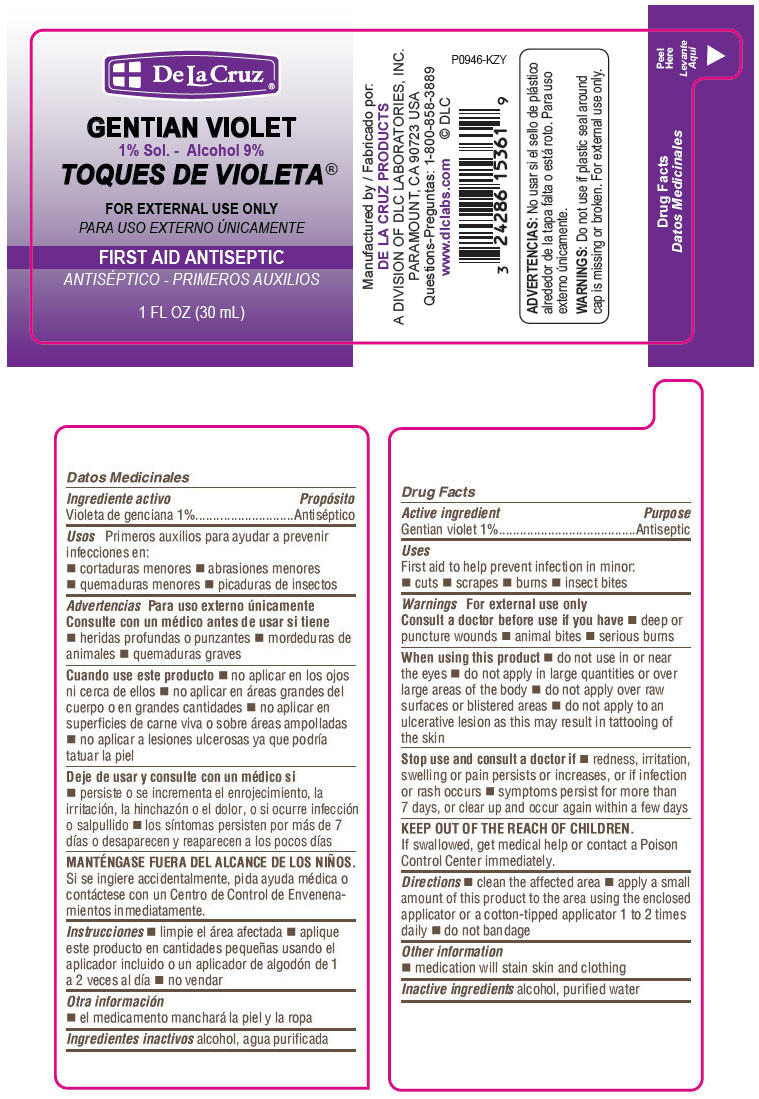 DRUG LABEL: DE LA CRUZ GENTIAN VIOLET
NDC: 24286-1531 | Form: TINCTURE
Manufacturer: DLC Laboratories, Inc.
Category: otc | Type: HUMAN OTC DRUG LABEL
Date: 20241230

ACTIVE INGREDIENTS: GENTIAN VIOLET 1 g/100 mL
INACTIVE INGREDIENTS: ALCOHOL 10 mL/100 mL; WATER

DE LA CRUZ® GENTIAN VIOLET 1%

Drug Facts

Active ingredient

Gentian violet 1%

Purpose

Antiseptic

Uses

First aid to help prevent infection in minor:

- cuts
- scrapes
- burns
- insect bites

Warnings

For external use only

Consult a doctor before use if you have

- deep or puncture wounds
- animal bites
- serious burns

When using this product

- do not use in or near the eyes or over large areas of the body
- do not apply to an ulcerative lesion as this may result in tattooing of the skin

Stop use and consult a doctor if

- redness, irritation, swelling or pain persists or increases, or if infection or rash occurs
- symptoms persist for more than 7 days, or clear up and occur again within a few days

KEEP OUT OF REACH OF CHILDREN

KEEP OUT OF THE REACH OF CHILDREN. If swallowed, get medical help or contact a Poison Control Center immediately.

Directions

- clean the affected area
- apply a small amount of this product to the area using the enclosed applicator or a cotton-tipped applicator 1 to 2 times daily
- do not bandage

Other information

- medication will stain skin and clothing

Inactive ingredients

alcohol, purified water

Questions

1-800-858-3889

Manufactured by
DE LA CRUZ PRODUCTS
A DIVISION OF DLC LABORATORIES, INC.
PARAMOUNT, CA 90723 USA